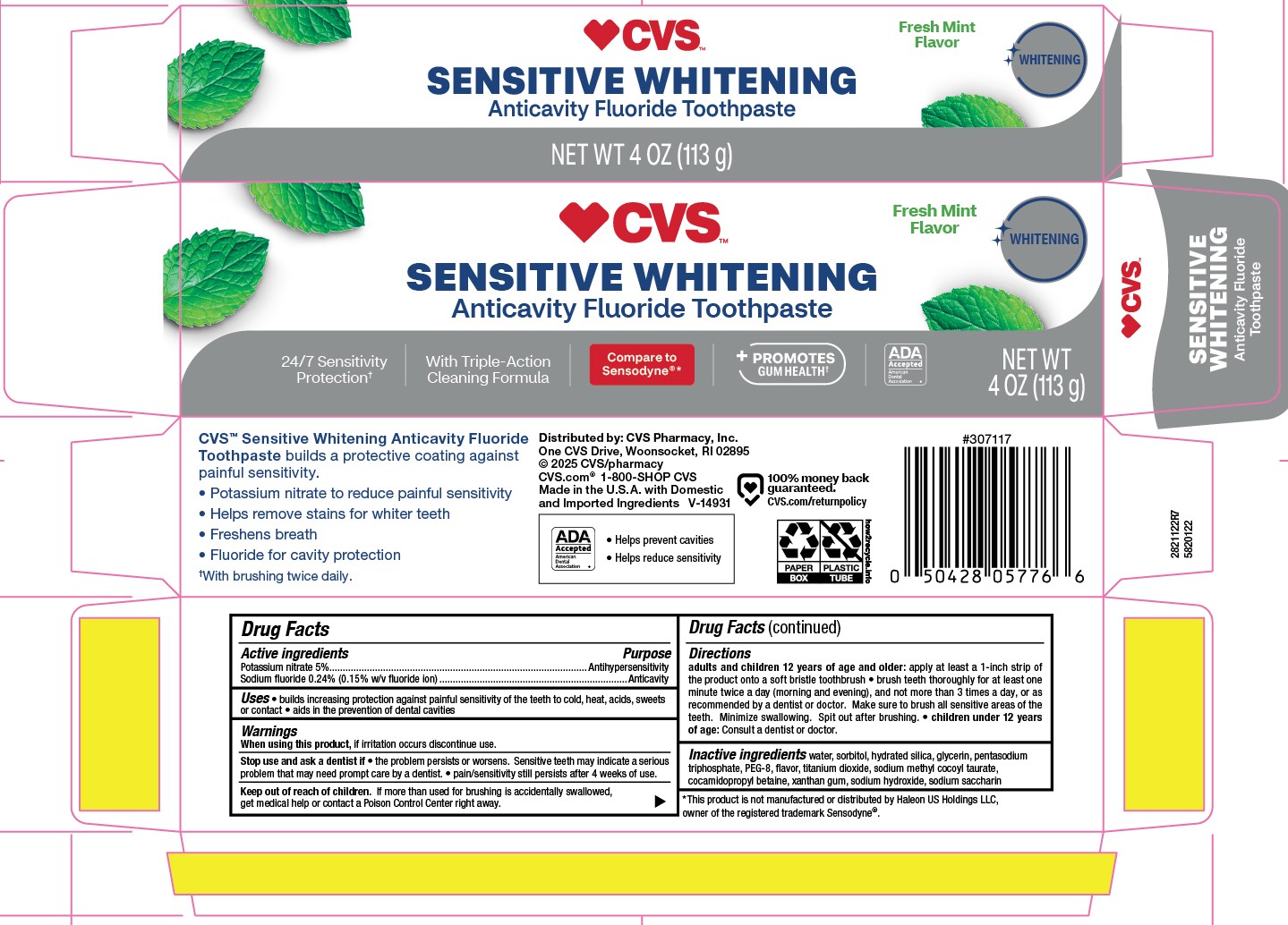 DRUG LABEL: CVS
NDC: 59779-122 | Form: PASTE, DENTIFRICE
Manufacturer: CVS Pharmacy
Category: otc | Type: HUMAN OTC DRUG LABEL
Date: 20251121

ACTIVE INGREDIENTS: SODIUM FLUORIDE 0.15 g/100 g; POTASSIUM NITRATE 5 g/100 g
INACTIVE INGREDIENTS: SACCHARIN SODIUM; WATER; PENTASODIUM TRIPHOSPHATE; POLYETHYLENE GLYCOL 400; SORBITOL; TITANIUM DIOXIDE; SODIUM HYDROXIDE; GLYCERIN; XANTHAN GUM; HYDRATED SILICA; COCAMIDOPROPYL BETAINE; SODIUM METHYL COCOYL TAURATE

5820122 CVS Sens Ex Whitening (8015201)

Active ingredients / Purpose

Potassium nitrate 5%....................................................Antihypersensitivity

Sodium fluoride 0.24% (0.15% w/v fluoride ion)............Anticavity

Uses

- builds increasing protection against painful sensitivity of the teeth to cold, heat, acids, sweets or contact
- aids in the prevention of dental cavities

Directions

Brush teeth thoroughly for at least one minute for at least twice a day (morning and evening), and not more than 3 times a day, or as recommended by a dentist or doctor. Make sure to brush all sensitive areas of the teeth. Minimiza swallowing. Spit out after brushing.

DOSAGE AND ADMINISTRATION

adults and children 12 years of age and older: apply at least a 1-inch strip of the product onto a soft bristle toothbrush.

- Children under 12 years of age: Consult a dentist or a doctor.

Other Information

Store in a cool dry place. Keep tube capped when not in use.

Inactive ingredients

water, sorbitol, hydrated silica, glycerin, pentasodium triphosphate, PEG-8, flavor, titanium dioxide, sodium methyl cocoyl taurate, cocamidopropyl betaine, xanthan gum, sodium hydroxide, sodium saccharin

When using this product

Stop use and ask a dentist if

- the problem persists or worsens. Sensitive teeth may indicate a serious problem that may need prompt care by a dentist.
- pain/sensitivity still persists after 4 weeks of use.

When using this product, if irritation occurs discontinue use.

Keep out of reach of children. If more than used for brushing is accidentally swallowed, get medical help or contact a Posion Control rgith away.